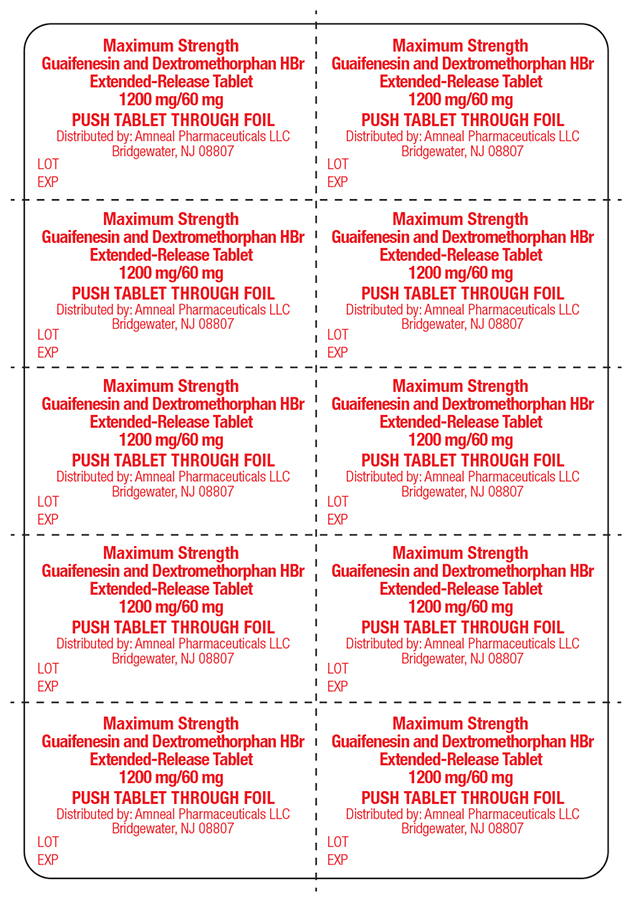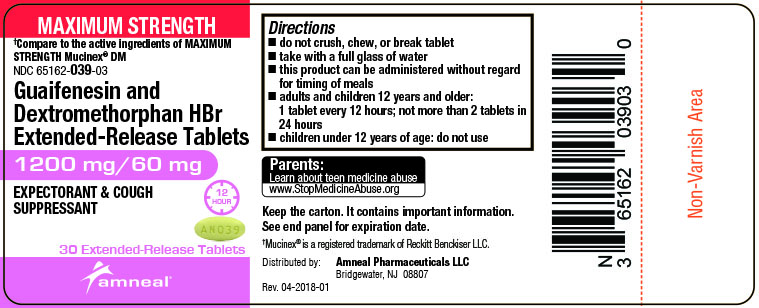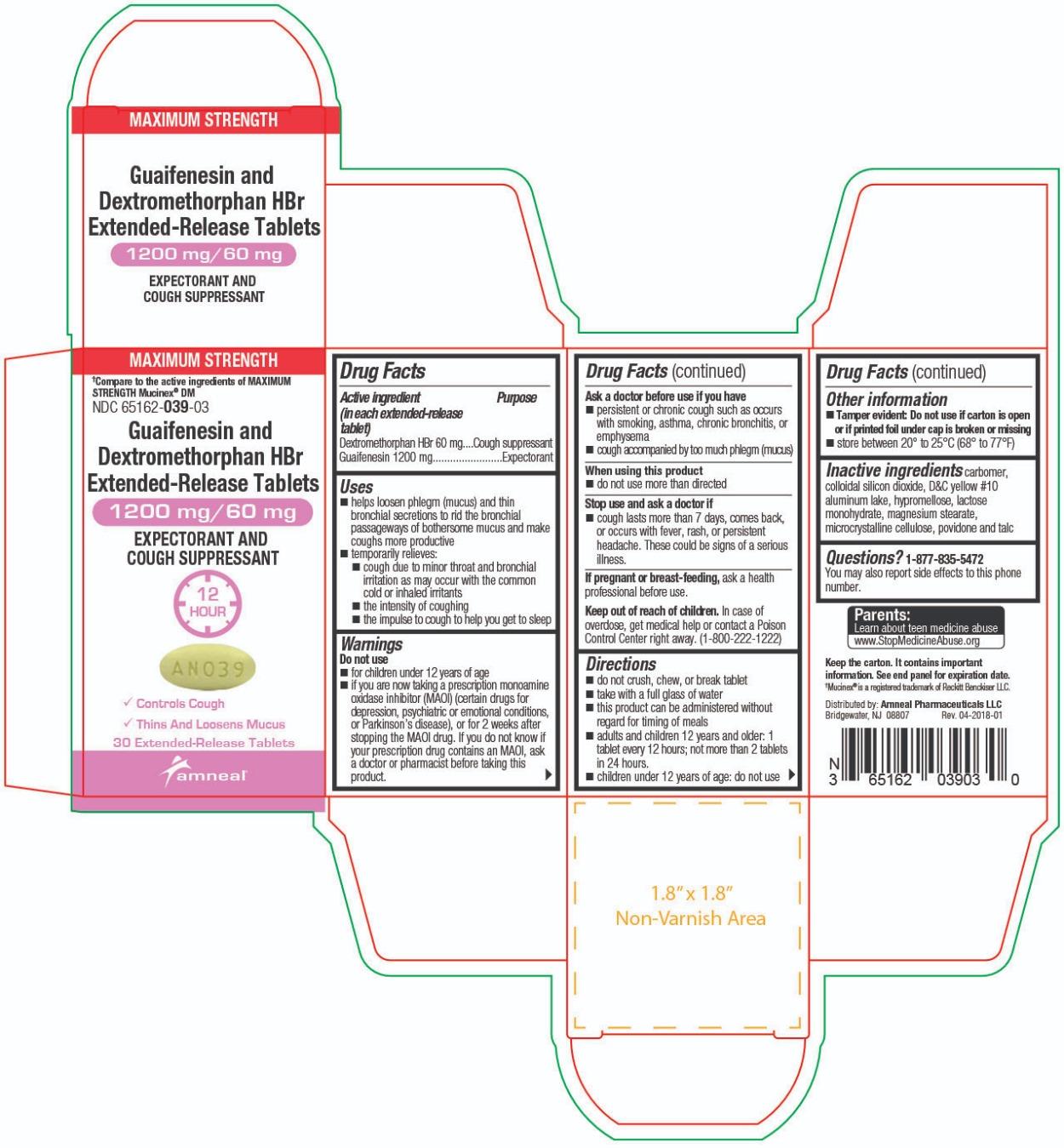 DRUG LABEL: Guaifenesin and Dextromethorphan HBr
NDC: 65162-039 | Form: TABLET, EXTENDED RELEASE
Manufacturer: Amneal Pharmaceuticals LLC
Category: otc | Type: HUMAN OTC DRUG LABEL
Date: 20241025

ACTIVE INGREDIENTS: GUAIFENESIN 1200 mg/1 1; DEXTROMETHORPHAN HYDROBROMIDE 60 mg/1 1
INACTIVE INGREDIENTS: CARBOMER HOMOPOLYMER TYPE A; SILICON DIOXIDE; D&C YELLOW NO. 10; HYPROMELLOSES; LACTOSE MONOHYDRATE; MAGNESIUM STEARATE; CELLULOSE, MICROCRYSTALLINE; TALC; POVIDONE

Guaifenesin and Dextromethorpham HBr Extended-Release Tablets, 1200 mg/60 mg
EXPECTORANT & COUGH SUPPRESSANT
Drug Facts

Active ingredient(s) (in each extended-release tablet)

Active ingredient (in each extended-release tablet)
Dextromethorphan HBr 60 mg

Guaifenesin 1200 mg

Purpose

Guaifenesin - Expectorant

Dextromethorphan HBr - Cough suppressant

Uses

- helps loosen phlegm (mucus) and thin bronchial secretions to rid the bronchial passageways of bothersome mucus and make coughs more productive
- temporarily relieves:
  - cough due to minor throat and bronchial irritation as may occur with the common cold or inhaled irritants
  - the intensity of coughing
  - the impulse to cough to help you get to sleep

Warnings

Do not use

- for children under 12 years of age
- if you are now taking a prescription monoamine oxidase inhibitor (MAOI) (certain drugs for depression, psychiatric or emotional conditions, or Parkinson’s disease), or for 2 weeks after stopping the MAOI drug. If you do not know if your prescription drug contains an MAOI, ask a doctor or pharmacist before taking this product.

Ask a doctor before use if you have

- persistent or chronic cough such as occurs with smoking, asthma, chronic bronchitis, or emphysema
- cough accompanied by too much phlegm (mucus)

When using this product

- do not use more than directed

Stop use and ask a doctor if

- cough lasts more than 7 days, comes back, or occurs with fever, rash, or persistent headache. These could be signs of a serious illness.

If pregnant or breast-feeding,

ask a health professional before use.

Keep out of reach of children.

In case of overdose, get medical help or contact a Poison Control Center right away. (1-800-222-1222)

Directions

1200 mg/60 mg

- do not crush, chew, or break tablet
- take with a full glass of water
- this product can be administered without regard for timing of meals
- adults and children 12 years and older: 1 tablet every 12 hours; not more than 2 tablets in 24 hours.
- children under 12 years of age: do not use

Other information

- Bottle: Tamper evident: Do not use if carton is open or if printed foil under cap is broken or missing
- Blister: Do not use if carton is open or if printed seal with product name on blister is broken or missing
- store between 20° to 25°C (68° to 77°F)

Inactive ingredients

carbomer, colloidal silicon dioxide, D&C yellow #10 aluminum lake, hypromellose, lactose monohydrate, magnesium stearate, microcrystalline cellulose, povidone and talc

Questions?

1-877-835-5472
You may also report side effects to this phone number.

Parents:
Learn about teen medicine abuse
www.StopMedicineAbuse.org

Keep the carton. It contains important information.
See end panel for expiration date.

†Mucinex® is a registered trademark of Reckitt Benckiser LLC.

Distributed by:
Amneal Pharmaceuticals LLC
Bridgewater, NJ 08807

Rev. 04-2018-01